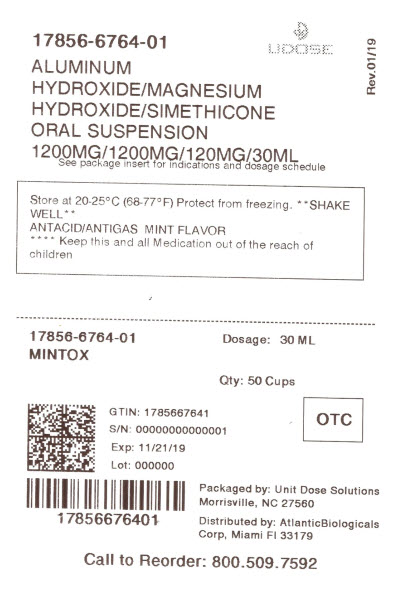 DRUG LABEL: mintox
NDC: 17856-6764 | Form: SUSPENSION
Manufacturer: ATLANTIC BIOLOGICALS CORP.
Category: otc | Type: HUMAN OTC DRUG LABEL
Date: 20210113

ACTIVE INGREDIENTS: ALUMINUM HYDROXIDE 400 mg/10 mL; MAGNESIUM HYDROXIDE 400 mg/10 mL; DIMETHICONE 40 mg/10 mL
INACTIVE INGREDIENTS: BUTYLPARABEN; HYPROMELLOSES; CELLULOSE, MICROCRYSTALLINE; CARBOXYMETHYLCELLULOSE SODIUM; PEPPERMINT OIL; PROPYLPARABEN; WATER; SACCHARIN SODIUM; SORBITOL; SILICON DIOXIDE

Major Pharmaceuticals Mintox™ Drug Facts

Active ingredients (in each 10 mL)

Aluminum hydroxide (equiv. to dried gel, USP) 400 mg

Magnesium hydroxide 400 mg

Simethicone 40 mg

Purpose

Antacid

Antigas

Uses

for the relief of

- acid indigestion
- heartburn
- sour stomach
- upset stomach associated with these symptoms
- pressure and bloating commonly referred to as gas

Warnings

Ask a doctor before use if you have

- kidney disease
- a magnesium-restricted diet

Ask a doctor or pharmacist before use if you are

presently taking a prescription drug. Antacids may interact with certain prescription drugs.

When using this product

do not take more than 80 mL in a 24-hour period, or use the maximum dosage for more than 2 weeks, except under the advice and supervision of a physician

Directions

- shake well before using
- only use the dose cup provided
- adults and children 12 years and older: take 10 mL to 20 mL four times a day or as directed by a physician
- do not take more than 80 mL in 24 hours or use the maximum dosage for more than 2 weeks
- children under 12 years: consult a physician

Other information

- each 10 mL contains: magnesium 175 mg
- does not meet USP requirements for preservative effectiveness
- store at 20-25ºC (68-77ºF)
- protect from freezing

Inactive ingredients

butylparaben, flavor, hypromellose, microcrystalline cellulose and carboxymethylcellulose sodium, peppermint oil, propylparaben, purified water, saccharin sodium, simethicone emulsion, sorbitol, sorbitol solution

Questions or comments?

1-800-616-2471

Principal Display Panel

Regluar Strength

Mintox™

Antacid/Antigas

Aluminum Hydroxide ■ Magnesium Hydroxide ■ Simethicone

Fast Relief of:

Heartburn

Acid Indigestion

Pressure and Bloating

Mint Flavor

Compare to the active ingredients of Maalox® Advanced

NDC 17856-6764-01